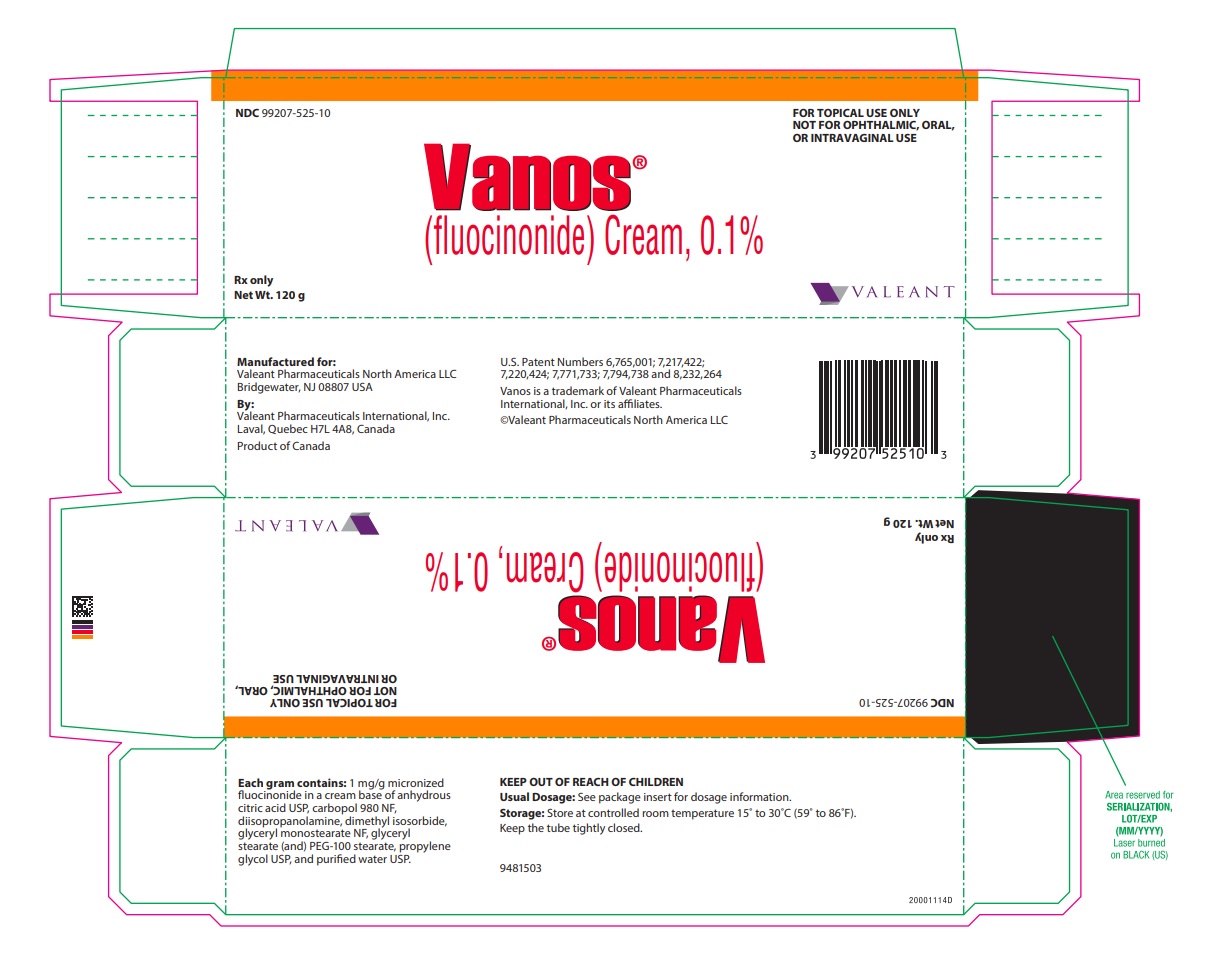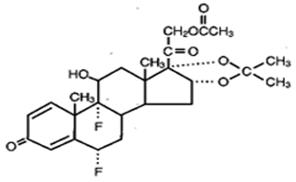 DRUG LABEL: Vanos
NDC: 99207-525 | Form: CREAM
Manufacturer: Bausch Health US, LLC
Category: prescription | Type: HUMAN PRESCRIPTION DRUG LABEL
Date: 20240227

ACTIVE INGREDIENTS: FLUOCINONIDE 1 mg/1 g
INACTIVE INGREDIENTS: ANHYDROUS CITRIC ACID; CARBOMER HOMOPOLYMER TYPE C (ALLYL PENTAERYTHRITOL CROSSLINKED); DIISOPROPANOLAMINE; DIMETHYL ISOSORBIDE; GLYCERYL MONOSTEARATE; PEG-100 STEARATE; PROPYLENE GLYCOL; WATER

HIGHLIGHTS OF PRESCRIBING INFORMATION

These highlights do not include all the information needed to use VANOS Cream safely and effectively. See full prescribing information for VANOS Cream.
VANOS® (fluocinonide) Cream, 0.1%
For topical use
Initial U.S. Approval: 1971

1 INDICATIONS AND USAGE

VANOS Cream is a corticosteroid indicated for the relief of the inflammatory and pruritic manifestations of corticosteroid responsive dermatoses in patients 12 years of age or older. (1)

Limitation of Use:

- Treatment beyond 2 consecutive weeks is not recommended, and the total dosage should not exceed 60 g per week because of the potential for the drug to suppress the hypothalamic-pituitary-adrenal (HPA) axis. (1)
- Avoid use on the face, groin, or axillae. (1.2)
- Avoid use in perioral dermatitis or rosacea. (1.2)

2 DOSAGE AND ADMINISTRATION

For topical use only. VANOS Cream is not for ophthalmic, oral, or intravaginal use. (2)

Psoriasis: apply a thin layer once or twice daily to the affected skin areas. (2)

Atopic Dermatitis: apply a thin layer once daily to the affected skin areas. (2)

Corticosteroid Responsive Dermatoses, other than psoriasis or atopic dermatitis: apply a thin layer once or twice daily to the affected areas. (2)

3 DOSAGE FORMS AND STRENGTHS

Cream, 0.1% (3)

4 CONTRAINDICATIONS

None (4)

5 WARNINGS AND PRECAUTIONS

- VANOS Cream has been shown to suppress the HPA axis. Systemic absorption of VANOS Cream may produce reversible hypothalamic-pituitary-adrenal (HPA) axis suppression, Cushing's syndrome, hyperglycemia and unmask latent diabetes. (5.1)
- Systemic absorption may require evaluation for HPA-axis suppression. (5.1)
- Modify use should HPA-axis suppression develop. (5.1)
- Potent corticosteroids, use on large areas, prolonged use or occlusive use may increase systemic absorption. (5.3)
- Local adverse reactions with topical steroids may include atrophy, striae, irritation, acneiform eruptions, hypopigmentation, and allergic contact dermatitis and may be more likely to occur with occlusive use or more potent corticosteroids. (5.3)
- Children may be more susceptible to systemic toxicity when treated with topical corticosteroids. (5.1, 8.4)

6 ADVERSE REACTIONS

The most commonly reported adverse reactions (≥1%) were headache, application site burning, nasopharyngitis, and nasal congestion. (6)

To report SUSPECTED ADVERSE REACTIONS, contact Valeant Pharmaceuticals North America LLC at 1-800-321-4576 or FDA at 1-800-FDA-1088 or www.fda.gov/medwatch.

FULL PRESCRIBING INFORMATION

1 INDICATIONS AND USAGE

1.1 Indications

VANOS® (fluocinonide) Cream, 0.1% is indicated for the relief of the inflammatory and pruritic manifestations of corticosteroid responsive dermatoses in patients 12 years of age or older [see Use in Specific Populations (8.4)].

1.2 Limitation of Use

Treatment beyond 2 consecutive weeks is not recommended and the total dosage should not exceed 60 g per week because the safety of VANOS Cream for longer than 2 weeks has not been established and because of the potential for the drug to suppress the hypothalamic-pituitary-adrenal (HPA) axis. Therapy should be discontinued when control of the disease is achieved. If no improvement is seen within 2 weeks, reassessment of the diagnosis may be necessary. Do not use more than half of the 120 g tube per week.

VANOS Cream should not be used in the treatment of rosacea or perioral dermatitis, and should not be used on the face, groin, or axillae.

2 DOSAGE AND ADMINISTRATION

For topical use only. VANOS Cream is not for ophthalmic, oral, or intravaginal use.

For psoriasis, apply a thin layer of VANOS Cream once or twice daily to the affected skin areas as directed by a physician. Twice-daily application for the treatment of psoriasis has been shown to be more effective in achieving treatment success during 2 weeks of treatment.

For atopic dermatitis, apply a thin layer of VANOS Cream once daily to the affected skin areas as directed by a physician. Once-daily application for the treatment of atopic dermatitis has been shown to be as effective as twice daily treatment in achieving treatment success during 2 weeks of treatment [see Clinical Studies (14)].

For corticosteroid responsive dermatoses, other than psoriasis or atopic dermatitis, apply a thin layer of VANOS Cream once or twice daily to the affected areas as directed by a physician.

3 DOSAGE FORMS AND STRENGTHS

Cream, 0.1%.

Each gram of VANOS Cream contains 1 mg of fluocinonide in a white to off-white cream base.

4 CONTRAINDICATIONS

None.

5 WARNINGS AND PRECAUTIONS

5.1 Effect on Endocrine System

Systemic absorption of topical corticosteroids, including VANOS Cream, can produce reversible hypothalamic-pituitary-adrenal (HPA) axis suppression with the potential for clinical glucocorticosteroid insufficiency. This may occur during treatment or upon withdrawal of the topical corticosteroid. In addition, the use of VANOS Cream for longer than 2 weeks may suppress the immune system [see Nonclinical Toxicology (13.1)].

HPA-axis suppression has been observed with VANOS Cream, 0.1% applied once or twice daily in 2 out of 18 adult patients with plaque-type psoriasis, 1 out of 31 adult patients with atopic dermatitis, and 4 out of 123 pediatric patients with atopic dermatitis [see Use in Specific Populations (8.4) and Clinical Pharmacology (12.2)].

Because of the potential for systemic absorption, use of topical corticosteroids, including VANOS Cream, may require that patients be periodically evaluated for HPA-axis suppression. Factors that predispose a patient using a topical corticosteroid to HPA-axis suppression include the use of more potent steroids, use over large surface areas, use over prolonged periods, use under occlusion, use on an altered skin barrier, and use in patients with liver failure.

An adrenocorticotropic hormone (ACTH) stimulation test may be helpful in evaluating patients for HPA-axis suppression. If HPA-axis suppression is documented, an attempt should be made to gradually withdraw the drug, to reduce the frequency of application, or to substitute a less potent steroid. Manifestations of adrenal insufficiency may require supplemental systemic corticosteroids. Recovery of HPA-axis function is generally prompt and complete upon discontinuation of topical corticosteroids.

Cushing's syndrome, hyperglycemia, and unmasking of latent diabetes mellitus can also result from systemic absorption of topical corticosteroids.

Use of more than one corticosteroid-containing product at the same time may increase the total systemic absorption of topical corticosteroids.

Studies conducted in pediatric patients demonstrated reversible HPA-axis suppression after use of VANOS Cream. Pediatric patients may be more susceptible than adults to systemic toxicity from equivalent doses of VANOS Cream due to their larger skin surface-to-body-mass ratios [see Use in Specific Populations (8.4)].

5.2 Local Adverse Reactions with Topical Corticosteroids

Local adverse reactions may be more likely to occur with occlusive use, prolonged use, or use of higher potency corticosteroids. Reactions may include atrophy, striae, telangiectasis, burning, itching, irritation, dryness, folliculitis, acneiform eruptions, hypopigmentation, perioral dermatitis, allergic contact dermatitis, secondary infection, and miliaria. Some local adverse reactions may be irreversible.

5.3 Concomitant Skin Infections

If concomitant skin infections are present or develop, an appropriate antifungal or antibacterial agent should be used. If a favorable response does not occur promptly, use of VANOS Cream should be discontinued until the infection has been adequately controlled.

5.4 Allergic Contact Dermatitis

If irritation develops, VANOS Cream should be discontinued and appropriate therapy instituted. Allergic contact dermatitis with corticosteroids is usually diagnosed by observing failure to heal rather than noting a clinical exacerbation as with most topical products not containing corticosteroids. Such an observation should be corroborated with appropriate diagnostic patch testing.

6 ADVERSE REACTIONS

6.1 Clinical Trials Experience

Because clinical studies are conducted under widely varying conditions, adverse reaction rates observed in the clinical studies of a drug cannot be directly compared to rates in the clinical studies of another drug and may not reflect the rates observed in practice.

In clinical trials, a total of 443 adult subjects with atopic dermatitis or plaque-type psoriasis were treated once daily or twice daily with VANOS Cream for 2 weeks. The most commonly observed adverse reactions in these clinical trials were as follows:

Table 1: Most Commonly Observed Adverse Reactions (≥1%) in Adult Clinical Trials
Adverse Reaction | VANOS Cream, once daily (n=216) | VANOS Cream, twice daily (n=227) | Vehicle Cream, once or twice daily (n=211)
Headache | 8 (3.7%) | 9 (4.0%) | 6 (2.8%)
Application Site Burning | 5 (2.3%) | 4 (1.8%) | 14 (6.6%)
Nasopharyngitis | 2 (0.9%) | 3 (1.3%) | 3 (1.4%)
Nasal Congestion | 3 (1.4%) | 1 (0.4%) | 0

Safety in patients 12 to 17 years of age was similar to that observed in adults.

6.2 Postmarketing Experience

The following adverse reactions have been identified during postapproval use of VANOS Cream:

- Administration Site Conditions:discoloration, erythema, irritation, pruritus, swelling, pain, and condition aggravated.
- Immune System Disorders:hypersensitivity.
- Nervous System Disorders:headache and dizziness.
- Skin and Subcutaneous Tissue Disorders:acne, dry skin, rash, skin exfoliation, and skin tightness.

Because these reactions are reported voluntarily from a population of uncertain size, it is not always possible to reliably estimate their frequency or establish a causal relationship to drug exposure.

8 USE IN SPECIFIC POPULATIONS

8.1 Pregnancy

Teratogenic Effects: Pregnancy Category C

There are no adequate and well-controlled studies in pregnant women. Therefore, VANOS Cream should be used during pregnancy only if the potential benefit justifies the potential risk to the fetus.

Corticosteroids have been shown to be teratogenic in laboratory animals when administered systemically at relatively low dosage levels. Some corticosteroids have been shown to be teratogenic after dermal application in laboratory animals.

8.3 Nursing Mothers

Systemically administered corticosteroids appear in human milk and could suppress growth, interfere with endogenous corticosteroid production, or cause other untoward effects. It is not known whether topical administration of corticosteroids could result in sufficient systemic absorption to produce detectable quantities in breast milk. Nevertheless, a decision should be made whether to discontinue nursing or to discontinue the drug, taking into account the importance of the drug to the mother.

8.4 Pediatric Use

Safety and efficacy of VANOS Cream in pediatric patients younger than 12 years of age have not been established; therefore, use in pediatric patients younger than 12 years of age is not recommended.

HPA-axis suppression was studied in four sequential cohorts of pediatric patients with atopic dermatitis covering at least 20% of the body surface area (BSA), treated once daily or twice daily with VANOS Cream. The first cohort of 31 patients (mean 36.3% BSA) 12 to <18 years old; the second cohort included 31 patients (mean 39.0% BSA) 6 to <12 years old; the third cohort included 30 patients (mean 34.6% BSA) 2 to <6 years old; the fourth cohort included 31 patients (mean 40.0% BSA) 3 months to <2 years old. VANOS Cream caused HPA-axis suppression in 1 patient in the twice-daily group in Cohort 1, 2 patients in the twice-daily group in Cohort 2, and 1 patient in the twice-daily group in Cohort 3. Follow-up testing 14 days after treatment discontinuation, available for all 4 suppressed patients, demonstrated a normally responsive HPA axis. Signs of skin atrophy were present at baseline and severity was not determined, making it difficult to assess local skin safety. Therefore, the safety of VANOS Cream in patients younger than 12 years of age has not been demonstrated [see Warnings and Precautions (5.2)].

HPA-axis suppression has not been evaluated in patients with psoriasis who are less than 18 years of age.

Because of a higher ratio of skin surface area to body mass, pediatric patients are at a greater risk than adults of HPA-axis suppression and Cushing’s syndrome when they are treated with topical corticosteroids. They are therefore also at greater risk of adrenal insufficiency during or after withdrawal of treatment. Adverse effects including striae have been reported with inappropriate use of topical corticosteroids in infants and children.

HPA-axis suppression, Cushing’s syndrome, linear growth retardation, delayed weight gain, and intracranial hypertension have been reported in children receiving topical corticosteroids. Manifestations of adrenal suppression in children include low plasma cortisol levels and absence of response to cosyntropin (ACTH 1-24) stimulation. Manifestations of intracranial hypertension include bulging fontanelles, headaches, and bilateral papilledema.

8.5 Geriatric Use

Clinical studies of VANOS Cream did not include sufficient numbers of subjects aged 65 and over to determine whether they respond differently from younger subjects.

10 OVERDOSAGE

Topically applied VANOS Cream can be absorbed in sufficient amounts to produce systemic effects [see Warnings and Precautions (5.1)].

11 DESCRIPTION

VANOS (fluocinonide) Cream, 0.1% contains fluocinonide, a synthetic corticosteroid for topical dermatologic use. The corticosteroids constitute a class of primarily synthetic steroids used topically as anti-inflammatory and antipruritic agents. Fluocinonide has the chemical name 6 alpha, 9 alpha-difluoro-11 beta, 21-dihydroxy-16 alpha, 17 alpha-isopropylidenedioxypregna-1, 4-diene-3,20-dione 21-acetate. Its chemical formula is C26H32F2O7 and it has a molecular weight of 494.58.

It has the following chemical structure:

Fluocinonide is an almost odorless white to creamy white crystalline powder. It is practically insoluble in water and slightly soluble in ethanol.

Each gram of VANOS Cream contains 1 mg micronized fluocinonide in a cream base of anhydrous citric acid USP, carbopol 980 NF, diisopropanolamine, dimethyl isosorbide, glyceryl monostearate NF, glyceryl stearate (and) PEG-100 stearate, propylene glycol USP, and purified water USP.

12 CLINICAL PHARMACOLOGY

12.1 Mechanism of Action

Corticosteroids play a role in cellular signaling, immune function, inflammation, and protein regulation; however, the precise mechanism of action of VANOS Cream in corticosteroid responsive dermatoses is unknown.

12.2 Pharmacodynamics

Vasoconstrictor studies performed with VANOS Cream in healthy subjects indicate that it is in the super-high range of potency as compared with other topical corticosteroids; however, similar blanching scores do not necessarily imply therapeutic equivalence.

Application of VANOS Cream twice daily for 14 days in 18 adult subjects with plaque-type psoriasis (10–50% BSA, mean 19.6% BSA) and 31 adult subjects (17 treated once daily; 14 treated twice daily) with atopic dermatitis (2–10% BSA, mean 5% BSA) showed demonstrable HPA-axis suppression in 2 subjects with psoriasis (with 12% and 25% BSA) and 1 subject with atopic dermatitis (treated once daily, 4% BSA) where the criterion for HPA-axis suppression is a serum cortisol level of less than or equal to 18 micrograms per deciliter 30 minutes after stimulation with cosyntropin (ACTH1-24) [see Warnings and Precautions (5.1)].

HPA-axis suppression following application of VANOS Cream, 0.1% (once or twice daily) was also evaluated in 123 pediatric patients from 3 months to <18 years of age with atopic dermatitis (mean BSA range 34.6%-40.0%). HPA-axis suppression was observed in 4 patients in the twice-daily groups. Follow-up testing 14 days after treatment discontinuation demonstrated a normally responsive HPA axis in all 4 suppressed patients [see Warnings and Precautions (5.1) and Use in Specific Populations (8.4)].

12.3 Pharmacokinetics

The extent of percutaneous absorption of topical corticosteroids is determined by many factors including the vehicle and the integrity of the epidermal barrier. Topical corticosteroids can be absorbed from normal intact skin. Inflammation and/or other disease processes in the skin may increase percutaneous absorption.

13 NONCLINICAL TOXICOLOGY

13.1 Carcinogenesis, Mutagenesis, Impairment of Fertility

Long-term animal studies have not been performed to evaluate the carcinogenic potential of VANOS Cream because of severe immunosuppression induced in a 13-week dermal rat study. The effects of fluocinonide on fertility have not been evaluated.

Fluocinonide revealed no evidence of mutagenic or clastogenic potential based on the results of two in vitro genotoxicity tests (Ames test and chromosomal aberration assay using human lymphocytes). However, fluocinonide was positive for clastogenic potential when tested in the in vivo mouse micronucleus assay.

Topical (dermal) application of 0.0003%–0.03% fluocinonide cream to rats once daily for 13 weeks resulted in a toxicity profile generally associated with long-term exposure to corticosteroids including decreased skin thickness, adrenal atrophy, and severe immunosuppression. A NOAEL could not be determined in this study. In addition, topical (dermal) application of 0.1% fluocinonide cream plus ultraviolet radiation (UVR) exposure to hairless mice for 13 weeks and 150–900 mg/kg/day of 0.1% fluocinonide cream to minipigs (a model which more closely approximates human skin) for 13 weeks produced glucocorticoid-related suppression of the HPA axis, with some signs of immunosuppression noted in the dermal minipig study. Although the clinical relevance of the findings in animals to humans is not clear, sustained glucocorticoid-related immune suppression may increase the risk of infection and possibly the risk for carcinogenesis.

Topical doses of 0% (fluocinonide cream vehicle), 0.0001%, 0.005%, and 0.001% fluocinonide cream were evaluated in a 52-week dermal photocarcinogenicity study (40 weeks of treatment followed by 12 weeks of observation) conducted in hairless albino mice with concurrent exposure to low level ultraviolet radiation. Topical treatment with increasing concentrations of fluocinonide cream did not have an adverse effect in this study. The results of this study suggest that topical treatment with VANOS Cream would not enhance photocarcinogenesis.

14 CLINICAL STUDIES

Two adequate and well-controlled efficacy and safety studies of VANOS Cream have been completed, one in adult subjects with plaque-type psoriasis (Table 2), and one in adult subjects with atopic dermatitis (Table 3). In each of these studies, subjects with between 2% and 10% body surface area involvement at baseline treated all affected areas either once daily or twice daily with VANOS Cream for 14 consecutive days. The primary measure of efficacy was the proportion of subjects whose condition was cleared or almost cleared at the end of treatment. The results of these studies are presented in the tables below as percent and number of patients achieving treatment success at Week 2.

Table 2: Plaque-type Psoriasis in Adults
 | VANOS Cream, once daily (n=107) | Vehicle, once daily (n=54) | VANOS Cream, twice daily (n=107) | Vehicle, twice daily (n=55)
Subjects cleared | 0 (0) | 0 (0) | 6 (6%) | 0 (0)
Subjects achieving treatment success [Cleared or almost cleared] | 19 (18%) | 4 (7%) | 33 (31%) | 3 (5%)

Table 3: Atopic Dermatitis in Adults
 | VANOS Cream, once daily (n=109) | Vehicle, once daily (n=50) | VANOS Cream, twice daily (n=102) | Vehicle, twice daily (n=52)
Subjects cleared | 11 (10%) | 0 (0) | 17 (17%) | 0 (0)
Subjects achieving treatment success [Cleared or almost cleared] | 64 (59%) | 6 (12%) | 58 (57%) | 10 (19%)

No efficacy studies have been conducted to compare VANOS (fluocinonide) Cream, 0.1% with any other topical corticosteroid product, including fluocinonide cream 0.05%.

16 HOW SUPPLIED/STORAGE AND HANDLING

VANOS® (fluocinonide) Cream, 0.1% is white to off-white in color and is supplied in tubes as follows:

- 30 g NDC 99207-525-30
  60 g NDC 99207-525-60
  120 g NDC 99207-525-10

STORAGE AND HANDLING

Store at controlled room temperature 15° to 30°C (59° to 86°F).

Keep the tube tightly closed.

17 PATIENT COUNSELING INFORMATION

Advise the patient to read the FDA-approved patient labeling (Patient Information).

Patients using VANOS Cream should receive the following information and instructions. This information is intended to aid in the safe and effective use of this medication. It is not a disclosure of all possible adverse or unintended effects:

- VANOS Cream is to be used as directed by the physician. It is for external use only. Avoid contact with the eyes. It should not be used on the face, groin, and underarms.
- VANOS Cream should not be used for any disorder other than that for which it was prescribed.
- The treated skin area should not be bandaged or otherwise covered or wrapped, so as to be occlusive unless directed by the physician.
- Patients should report to their physician any signs of local adverse reactions.
- Other corticosteroid-containing products should not be used with VANOS Cream without first talking to the physician.
- As with other corticosteroids, therapy should be discontinued when control is achieved. If no improvement is seen in 2 weeks, the patient should be instructed to contact a physician. The safety of the use of VANOS Cream for longer than 2 weeks has not been established.
- Patients should be informed to not use more than 60 g per week of VANOS Cream. Do not use more than half of the 120 g tube per week.
- Patients should inform their physicians that they are using VANOS Cream if surgery is contemplated.
- Patients should wash their hands after applying medication.

Manufactured for:
Valeant Pharmaceuticals North America LLC
Bridgewater, NJ 08807 USA

By:
Valeant Pharmaceuticals International, Inc.
Laval, Quebec H7L 4A8, Canada

U.S. Patent Numbers 6,765,001; 7,217,422; 7,220,424; 7,771,733; 7,794,738 and 8,232,264

Vanos is a trademark of Valeant Pharmaceuticals International, Inc. or its affiliates.

©Valeant Pharmaceuticals North America LLC

9481801

Patient Information

VANOS® (VAN-ōs) (fluocinonide) Cream, 0.1%

IMPORTANT: For skin use only. Do not get VANOS Cream in your eyes, mouth, or vagina. Not for use on the face, groin, or underarms.

Read the Patient Information that comes with VANOS Cream before you start using it and each time you get a refill. There may be new information. This leaflet does not take the place of talking to your doctor about your condition or treatment.

What is VANOS Cream?

VANOS Cream is a prescription corticosteroid medicine used on the skin (topical) to treat adults and children 12 years and older with certain skin conditions that cause red, flaky, and itchy skin.

- You should not use VANOS Cream for longer than 2 weeks in a row.
- You should not use more than 60 grams of VANOS Cream or more than half of the 120 gram tube in 1 week.
- VANOS Cream should not be used:
  - if you have skin swelling or redness on the nose or face (rosacea)
  - for a scaly or bumpy rash around your mouth (perioral dermatitis)
  - on your face, underarms, or groin area

It is not known if VANOS Cream is safe and effective in children under 12 years of age.

What should I tell my doctor before using VANOS Cream?

Before using VANOS Cream, tell your doctor if you:

- have had irritation or other skin reaction to a steroid medicine in the past
- adrenal gland problems
- plan to have surgery
- are pregnant or plan to become pregnant. It is not known if VANOS Cream will harm your unborn baby. Talk to your doctor if you are pregnant or plan to become pregnant.
- are breast-feeding or plan to breastfeed. It is not known if VANOS Cream passes into your breast milk. Talk to your doctor about the best way to feed your baby if you use VANOS Cream.

Tell your doctor about all the medicine you take including prescription and nonprescription medicines, vitamins, and herbal supplements. Especially tell your doctor if you take a corticosteroid medicine by mouth or use other products on your skin that contain corticosteroids. Ask your doctor or pharmacist if you are not sure.

Know the medicines you take. Keep a list of your medicines with you to show your doctor and pharmacist when you get a new medicine.

How should I use VANOS Cream?

- See “What is VANOS Cream?”
- Use VANOS Cream exactly as your doctor tells you.
- This medicine is for use on the skin only. Do not use VANOS Cream in your eyes, mouth, or vagina.
- Wash your hands after you use VANOS Cream.
- Do not use VANOS Cream for longer than 2 weeks in a row.
- Talk to your doctor if your skin does not get better after 2 weeks of treatment with VANOS Cream.
- Do not bandage or cover the skin treated with VANOS Cream unless your doctor tells you to.

What are the possible side effects with VANOS Cream?

VANOS Cream may cause side effects, including:

- Symptoms of a disorder where the adrenal gland does not make enough of certain hormones (adrenal insufficiency) during treatment or after stopping treatment. Your doctor may do blood tests to check you for adrenal insufficiency while you are using VANOS Cream. Tell your doctor if you have any of these symptoms of adrenal insufficiency:
  - tiredness that worsens and does not go away
  - nausea or vomiting
  - dizziness or fainting
  - muscle weakness
  - irritability and depression
  - loss of appetite
  - weight loss
- Cushing’s syndrome, when the body is exposed to too much of the hormone cortisol. Your doctor may do tests to check for this. Symptoms can include:
  - weight gain, especially around your upper back and midsection
  - slow healing of cuts, insect bites, and infections
  - tiredness and muscle weakness
  - depression, anxiety, and irritability
  - roundness of your face (moon face)
  - new or worsening high blood pressure

The most common side effect of VANOS Cream is burning of your skin treated with VANOS Cream.

Talk to your doctor about any side effect that bothers you or that does not go away.

These are not all the side effects with VANOS Cream. Ask your doctor or pharmacist for more information.

Call your doctor for medical advice about side effects. You may report side effects to FDA at 1-800-FDA-1088 or www.fda.gov/medwatch.

You may also report side effects to Valeant Pharmaceuticals North America LLC at 1-800-321-4576.

How should I store VANOS Cream?

- Store VANOS Cream at room temperature, between 59° to 86°F (15° to 30°C).
- Keep the tube tightly closed.

Keep VANOS Cream and all medicines out of reach of children.

General information about VANOS Cream
Medicines are sometimes prescribed for purposes other than those listed in the Patient Information leaflet. Do not use VANOS Cream for a condition for which it was not prescribed. Do not give VANOS Cream to other people, even if they have the same symptoms you have. It may harm them.

This Patient Information leaflet summarizes the most important information about VANOS Cream. If you would like more information, talk with your doctor. You can also ask your pharmacist or doctor for information about VANOS Cream that is written for healthcare professionals.

What are the ingredients in VANOS Cream?
Active ingredient: fluocinonide 0.1%

Inactive ingredients: anhydrous citric acid USP, carbopol 980 NF, diisopropanolamine, dimethyl isosorbide, glyceryl monostearate NF, glyceryl stearate (and) PEG-100 stearate, propylene glycol USP, and purified water USP.

This Patient Information has been approved by the U.S. Food and Drug Administration.

Manufactured for:
Valeant Pharmaceuticals North America LLC
Bridgewater, NJ 08807 USA

By:
Valeant Pharmaceuticals International, Inc.
Laval, Quebec H7L 4A8, Canada

U.S. Patent Numbers 6,765,001; 7,217,422; 7,220,424; 7,771,733; 7,794,738 and 8,232,264

Vanos is a trademark of Valeant Pharmaceuticals International, Inc. or its affiliates.

©Valeant Pharmaceuticals North America LLC

Rev. 05/2017

9481801

PRINCIPAL DISPLAY PANEL - 120 g Tube Carton

NDC99207-525-10

Vanos®
(fluocinonide) Cream, 0.1%

FOR TOPICAL USE ONLY
NOT FOR OPHTHALMIC, ORAL,
OR INTRAVAGINAL USE

Rx only
Net. Wt. 120 g

VALEANT

9481503